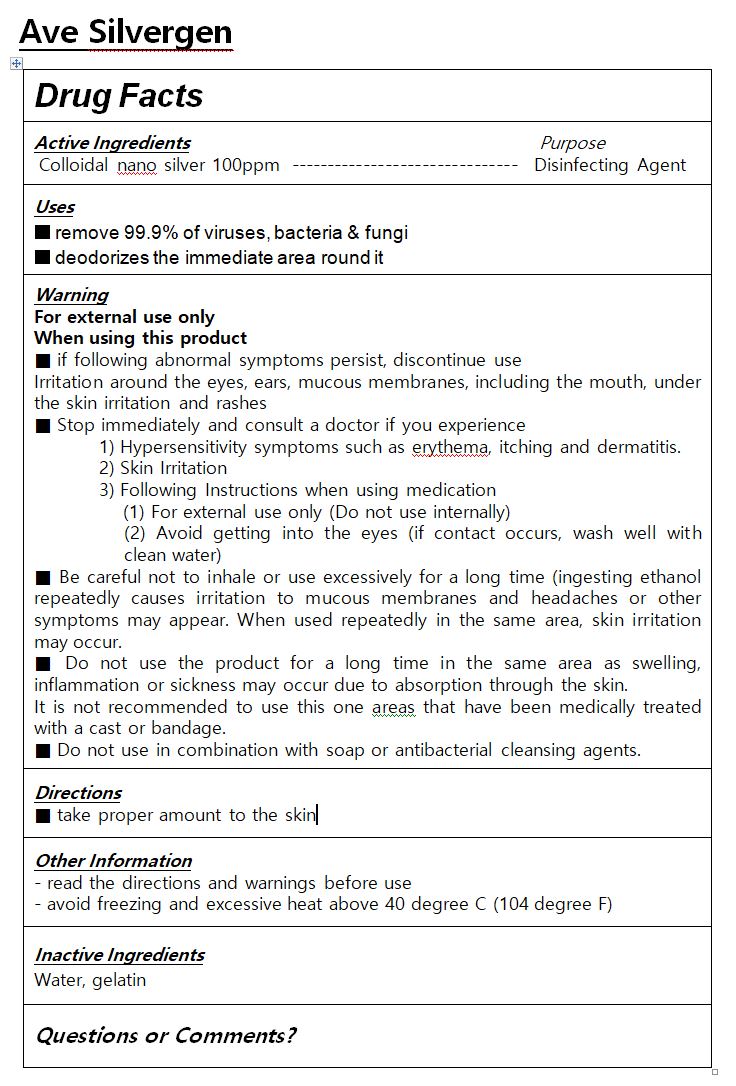 DRUG LABEL: Ave Silvergen
NDC: 81430-0004 | Form: SPRAY
Manufacturer: SCR CO.,LTD
Category: otc | Type: HUMAN OTC DRUG LABEL
Date: 20210213

ACTIVE INGREDIENTS: SILVER 0.0001 g/100 mL
INACTIVE INGREDIENTS: WATER

Drug Facts

ACTIVE INGREDIENT

colloidal nano silver

INACTIVE INGREDIENT

water, gelatin

PURPOSE

disinfectant

keep out of reach of the children

INDICATIONS AND USAGE

take proper amount to the skin

WARNINGS

1. For external use only.

1) Do not use over the wound and irritated skin with eczema or infections

2) Discontinue using the product if signs of irritations and/or rashes occur and seek professional medical help

2. Keep the cover closed tight after use

3. Do not put the left over contents back into the container to avoid deterioration

1) Avoid contact with eyes

2) Keep out of reach of children

3) Store in a cool and dry place, away from direct sun light

DOSAGE AND ADMINISTRATION

for external use only